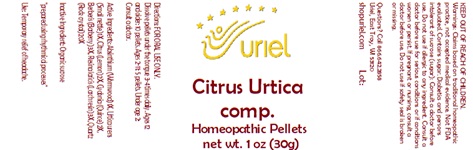 DRUG LABEL: Citrus Urtica comp.
NDC: 48951-3268 | Form: PELLET
Manufacturer: Uriel Pharmacy Inc.
Category: homeopathic | Type: HUMAN OTC DRUG LABEL
Date: 20240513

ACTIVE INGREDIENTS: WORMWOOD 1 [hp_X]/1 1; URTICA URENS 1 [hp_X]/1 1; LEMON 2 [hp_X]/1 1; QUINCE 2 [hp_X]/1 1; BERBERIS VULGARIS ROOT BARK 3 [hp_X]/1 1; LARIX DECIDUA RESIN 3 [hp_X]/1 1; SILICON DIOXIDE 20 [hp_X]/1 1
INACTIVE INGREDIENTS: SUCROSE

Citrus Urtica comp.

INDICATIONS AND USAGE

Directions: FOR ORAL USE ONLY.

DOSAGE AND ADMINISTRATION

Dissolve pellets under the tongue 3-4 times daily. Ages 12 and older: 10 pellets. Ages 2-11: 5 pellets. Under age 2: Consult a doctor.

ACTIVE INGREDIENT

Active Ingredients: Absinthium (Wormwood) 1X, Urtica urens (Small nettle) 1X, Citrus (Lemon) 2X, Cydonia (Quince) 2X, Berberis (Barberry) 3X, Resina laricis (Larch resin) 3X, Quartz (Rock crystal) 20X

Inactive Ingredient: Organic sucrose

"prepared using rhythmical processes"

PURPOSE

Use: Temporary relief of allergies.

KEEP OUT OF REACH OF CHILDREN.

WARNINGS

Warnings: Claims based on traditional homeopathic practice, not accepted medical evidence. Not FDA evaluated. Contains sugar. Diabetics and persons intolerant of sucrose (sugar): Consult a doctor before use. Do not use if allergic to any ingredient. Consult a doctor before use for serious conditions or if conditions worsen or persist. If pregnant or nursing, consult a doctor before use. Do not use if safety seal is broken or missing.

QUESTIONS

Questions? Call 866.642.2858 Uriel, East Troy, WI 53120 shopuriel.com Lot: